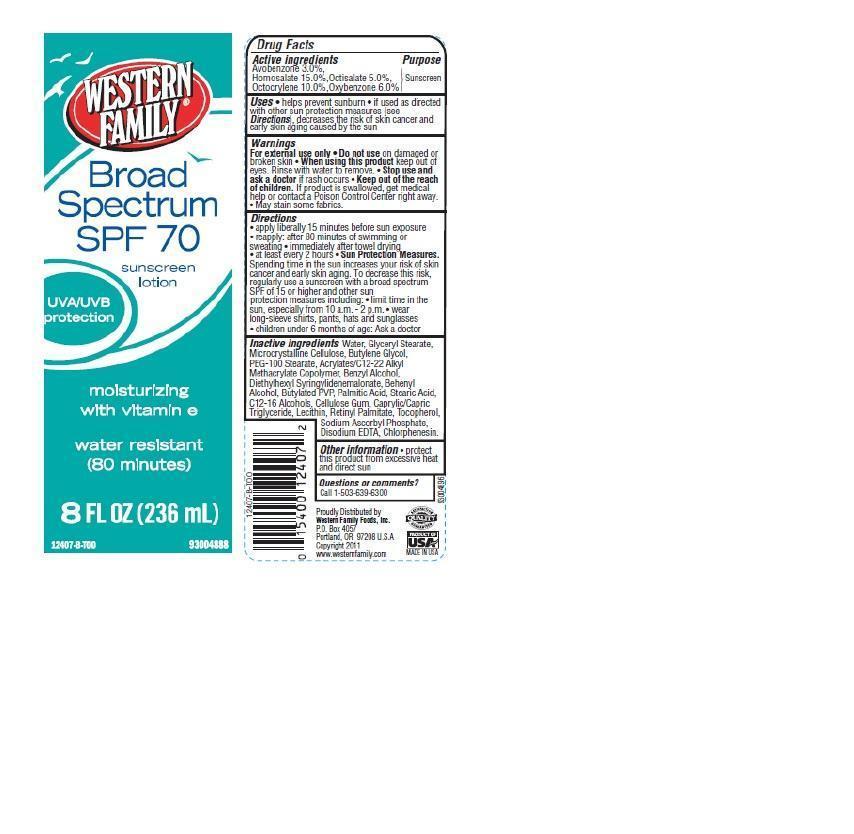 DRUG LABEL: Western Family Broad Spectrum Sunscreen
NDC: 55312-000 | Form: LOTION
Manufacturer: WESTERN FAMILY FOODS, INC.
Category: otc | Type: HUMAN OTC DRUG LABEL
Date: 20140303

ACTIVE INGREDIENTS: AVOBENZONE 3 g/100 g; HOMOSALATE 15 g/100 g; OCTISALATE 5 g/100 g; OCTOCRYLENE 10 g/100 g; OXYBENZONE 6 g/100 g
INACTIVE INGREDIENTS: WATER; GLYCERYL MONOSTEARATE; CELLULOSE, MICROCRYSTALLINE; BUTYLENE GLYCOL; PEG-100 STEARATE; BENZYL ALCOHOL; DIETHYLHEXYL SYRINGYLIDENEMALONATE; DOCOSANOL; PALMITIC ACID; STEARIC ACID; CARBOXYMETHYLCELLULOSE SODIUM; TRICAPRYLIN; VITAMIN A PALMITATE; TOCOPHEROL; SODIUM ASCORBYL PHOSPHATE; EDETATE DISODIUM; CHLORPHENESIN

Drug Facts

Active ingredients

Avobenzone 3.0%

Homosalate 15.0%

Octisalate 5.0%

Octocrylene 10.0%

Oxybenzone 6.0%

Purpose

Sunscreen

Uses

- helps prevent sunburn
- if used as directed with other sun protection measures(see directions) , decreases the risk of skin cancer and early skin aging caused by the sun

Warnings

For external use only

Do not use

on damaged or broken skin

When using this product

keep out of eyes. Rinse with water to remove.

Stop use and ask a doctor

if rash occurs

Keep out of the reach of children

If product is swallowed, get medical help or contact a Poison Control Center right away.

OTHER SAFETY INFORMATION

- May stain some fabrics.

Directions

- apply liberally 15 minutes before sun exposure
- reapply: after 80 minutes of swimming or sweating
- immediately after towel drying
- at least every 2 hours
- Sun Protection Measures.
- Spending time in the sun increases your risk of skin cancer and early skin aging. To decrease this risk, regularly use a sunscreen with a broad spectrum SPF of 15 or higher and other sun protection measures including
- limit time in the sun especially from 10 a.m. - 2 p.m.
- wear long-sleeve shirts, pants, hats and sunglasses
- children under 6 months of age: Ask a doctor

Inactive ingredients

Water, Glyceryl Stearate, Microcrystalline Cellulose, Butylene Glycol, PEG-100 Stearate, Acrylates/C12-22 Alkyl Methacrylate Copolymer, Benzyl Alcohol, Diethylhexyl Syringylidenemalonate, Behenyl Alcohol, Butylated PVP, Palmitic Acid, Stearic Acid, C12-16 Alcohols, Cellulose Gum, Caprylic/Capric Triglyceride, Lecithin, Retinyl Palmitate, Tocopherol, Sodium Ascorbyl Phosphate, Disodium EDTA, Chlorphenesin.

Other information

- protect this product from excessive heat and direct sun

Questions or comments?

Call 1-503-639-6300

Principal Display Panel

WESTERN FAMILY

Broad Spectrum SPF 70

sunscreen lotion

UVA/UVB protection

moisturizing with vitamin e

water resistant

(80 minutes)

8 FL OZ (236 mL)